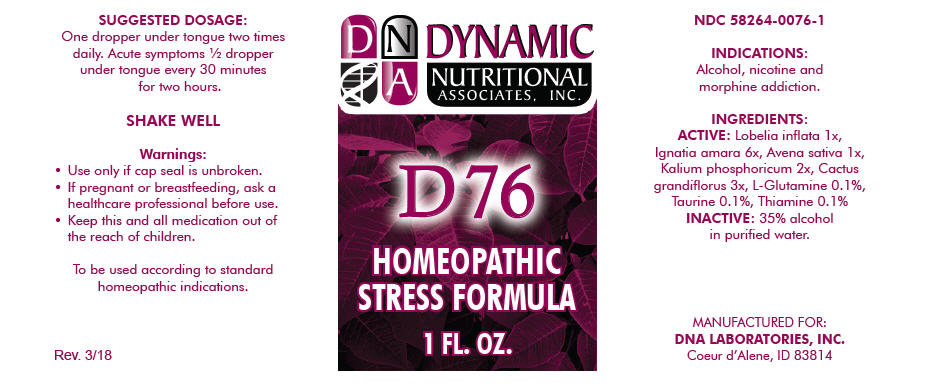 DRUG LABEL: D-76
NDC: 58264-0076 | Form: SOLUTION
Manufacturer: DNA Labs, Inc.
Category: homeopathic | Type: HUMAN OTC DRUG LABEL
Date: 20250113

ACTIVE INGREDIENTS: LOBELIA INFLATA 1 [hp_X]/1 mL; STRYCHNOS IGNATII SEED 6 [hp_X]/1 mL; AVENA SATIVA FLOWERING TOP 1 [hp_X]/1 mL; DIBASIC POTASSIUM PHOSPHATE 2 [hp_X]/1 mL; SELENICEREUS GRANDIFLORUS STEM 3 [hp_X]/1 mL; GLUTAMINE 4 [hp_X]/1 mL; TAURINE 4 [hp_X]/1 mL; THIAMINE HYDROCHLORIDE 4 [hp_X]/1 mL
INACTIVE INGREDIENTS: ALCOHOL; WATER

D-76

NDC 58264-0076-1

INDICATIONS

PURPOSE

Alcohol, nicotine and morphine addiction.

INGREDIENTS

ACTIVE

Lobelia inflata 1x, Ignatia amara 6x, Avena sativa 1x, Kalium phosphoricum 2x, Cactus grandiflorus 3x, L-Glutamine 0.1%, Taurine 0.1%, Thiamine 0.1%

INACTIVE

35% alcohol in purified water.

SUGGESTED DOSAGE

One dropper under tongue two times daily. Acute symptoms ½ dropper under tongue every 30 minutes for two hours.

STORAGE AND HANDLING

SHAKE WELL

Warnings

- Use only if cap seal is unbroken.

PREGNANCY OR BREAST FEEDING

- If pregnant or breastfeeding, ask a healthcare professional before use.

KEEP OUT OF REACH OF CHILDREN

- Keep this and all medication out of the reach of children.

To be used according to standard homeopathic indications.

PRINCIPAL DISPLAY PANEL - 1 FL. OZ. Bottle Label

DYNAMIC
NUTRITIONAL
ASSOCIATES, INC.

D 76

HOMEOPATHIC
STRESS FORMULA

1 FL. OZ.